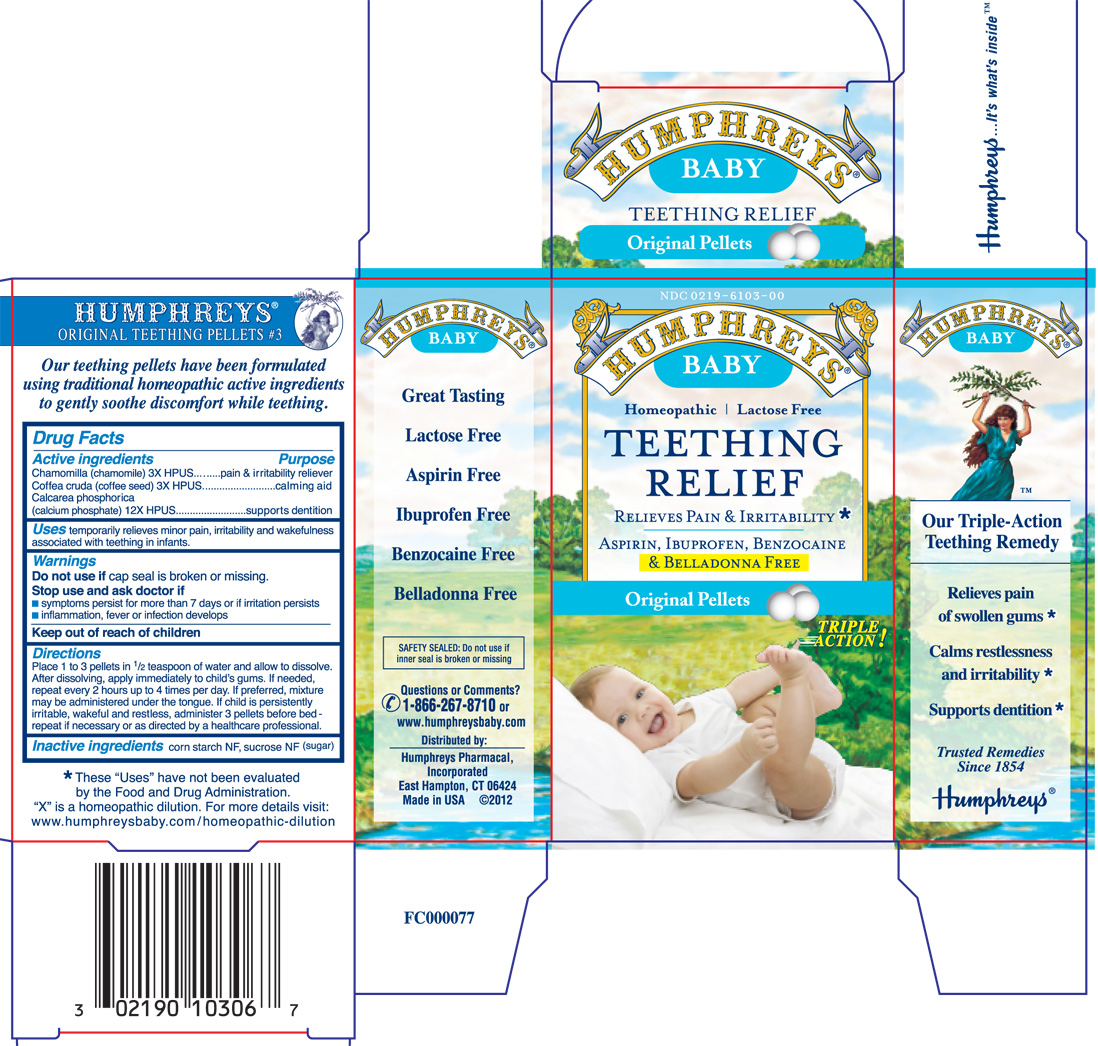 DRUG LABEL: Humphreys Baby Teething Relief Original
NDC: 0219-6103 | Form: PELLET
Manufacturer: Humphreys Pharmacal, Incorporated
Category: homeopathic | Type: HUMAN OTC DRUG LABEL
Date: 20121011

ACTIVE INGREDIENTS: matricaria recutita 3 [hp_X]/1 1; arabica coffee bean 3 [hp_X]/1 1; tribasic calcium phosphate 12 [hp_X]/1 1
INACTIVE INGREDIENTS: starch, corn; sucrose

Drug Facts

Active ingredients

Chamomilla (chamomile) 3X HPUS

Coffea cruda (coffee seed) 3X HPUS

Calcarea phosphorica (calcium phosphate) 12X HPUS

Purpose

Chamomilla (chamomile) 3X HPUS....................irritation reliever

Coffea cruda (coffee seed) 3X HPUS..................calming aid

Calcarea phosphorica (calcium phosphate) 12X....supports dentition

Uses

Temporarily relieves minor pain, irritability and wakefulness associated with teething in infants.

Warnings

Do not use if cap seal is broken or missing.

Stop use and ask doctor if

- symptoms persist for more than 7 days or if irritation persists
- inflammation, fever or infection develops

Keep out of reach of children

Directions

Place 1 to 3 pellets in 1/2 teaspoon of water and allow to dissolve.

After dissolving, apply immediately to child's gums. If needed, repeat every 2 hours

up to 4 times per day. If preferred, mixture may be administered under the tongue.

If child is persistently irritable wakeful and restless, administer 3 pellets before bed

- repeat if necessary or as directed by a healthcare professional.

Inactive ingredients

corn starch NF, sucrose NF (sugar)

Questions or Comments?

1-866-267-8710 or

www.humphreysbaby.com

Distributed by: Humphreys Pharmacal, Inc.

East Hampton, CT 06424

Made in USA